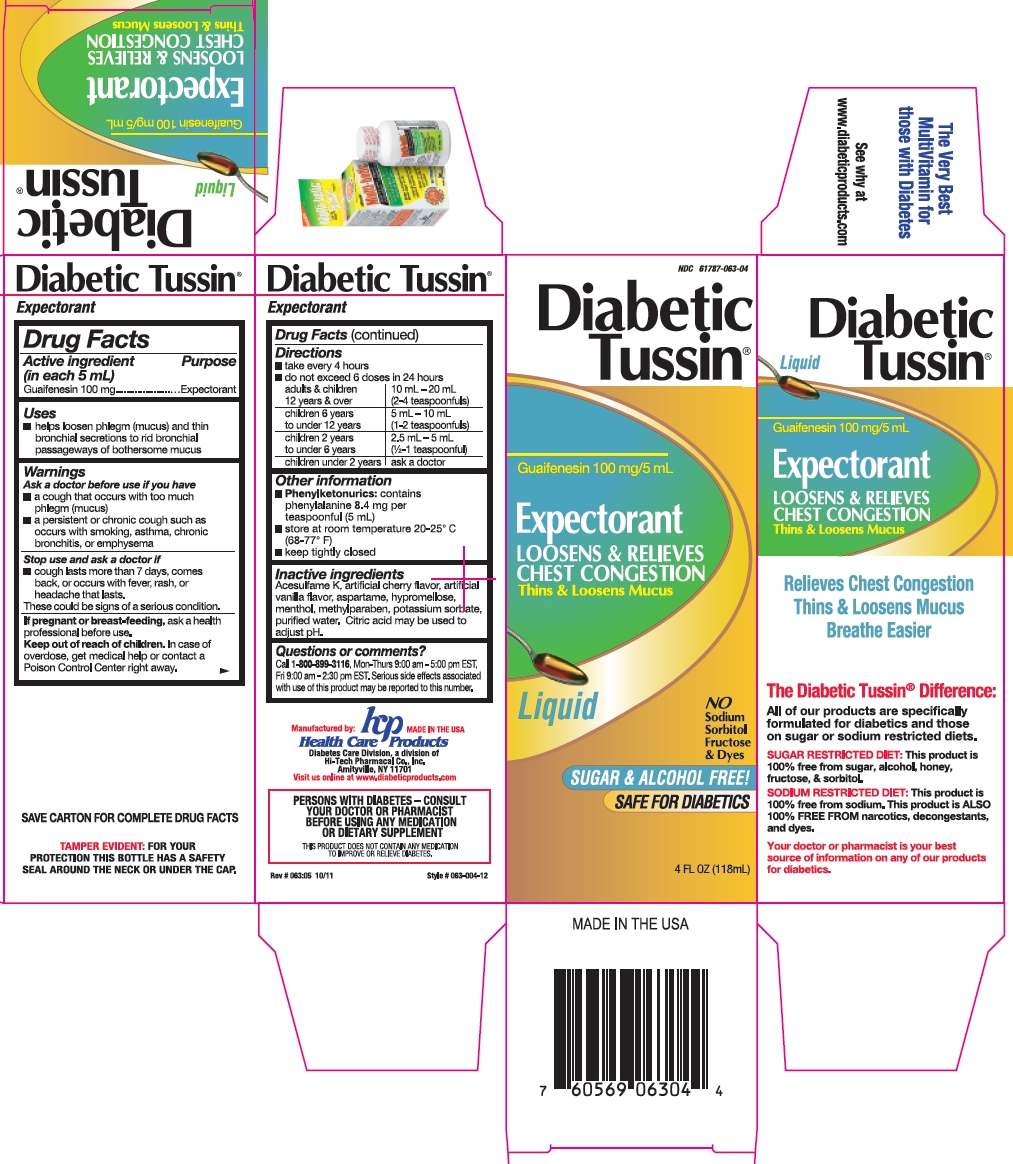 DRUG LABEL: Diabetic Tussin Expectorant
NDC: 61787-063 | Form: LIQUID
Manufacturer: Health Care Products
Category: otc | Type: HUMAN OTC DRUG LABEL
Date: 20191217

ACTIVE INGREDIENTS: GUAIFENESIN 100 mg/5 mL
INACTIVE INGREDIENTS: ACESULFAME POTASSIUM; ASPARTAME; HYPROMELLOSE, UNSPECIFIED; MENTHOL, UNSPECIFIED FORM; METHYLPARABEN; POTASSIUM SORBATE; WATER; ANHYDROUS CITRIC ACID

Drug Facts

Active ingredient (in each 5 mL)

Guaifenesin 100 mg

Purpose

Expectorant

Uses

- helps loosen phlegm (mucus) and thin bronchial secretions to rid bronchial passageways of bothersome mucus

Warnings

Ask a doctor before use if you have:

- a cough that occurs with too much phlegm (mucus)
- a persistent or chronic cough such as occurs with smoking, asthma, chronic bronchitis, or emphysema

Stop use and ask a doctor if:

- cough lasts more than 7 days, comes back, or occurs with fever, rash, or headache that lasts

These could be signs of a serious condition.

If pregnant or breast-feeding,

ask a health professional before use.

Keep out of reach of children.

In case of overdose, get medical help or contact a Poison Control Center right away.

Directions

- take every 4 hours
- do not exceed 6 doses in 24 hours

adults & children 12 years and over | 10 mL - 20 mL (2 - 4 teaspoonfuls)
children 6 years to under 12 years | 5 mL - 10 mL (1 - 2 teaspoonfuls)
children 2 years to under 6 years | 2.5 mL - 5 mL (½ - 1 teaspoonful)
children under 2 years | ask a doctor

Other information

- Phenylketonurics: contains phenylalanine 8.4 mg per teaspoonful (5 mL)
- store at room temperature 20-25°C (68-77°F).
- keep tightly closed.

Inactive ingredients

Acesulfame K, artificial cherry flavor, artificial vanilla flavor, aspartame, hypromellose, menthol, methylparaben, potassium sorbate, purified water. Citric acid may be used to adjust pH.

Questions or comments?

Call 1-800-899-3116, Mon-Thurs 9:00 am - 5:00 pm EST, Fri 9:00 am - 2:30 pm EST. Serious side effects associated with use of this product may be reported to this number.

Rev #063:05 10/11

Package/Label Principal Display Panel

NDC 61787-063-04

Diabetic Tussin®

Guaifenesin 100 mg/5 mL

Expectorant

Loosens & Relieves Chest Congestion

Thins & Loosens Mucus

Liquid

No Sodium, Sorbitol, Fructose & Dyes

SUGAR & ALCOHOL FREE!

SAFE FOR DIABETICS

4 FL OZ (118 mL)